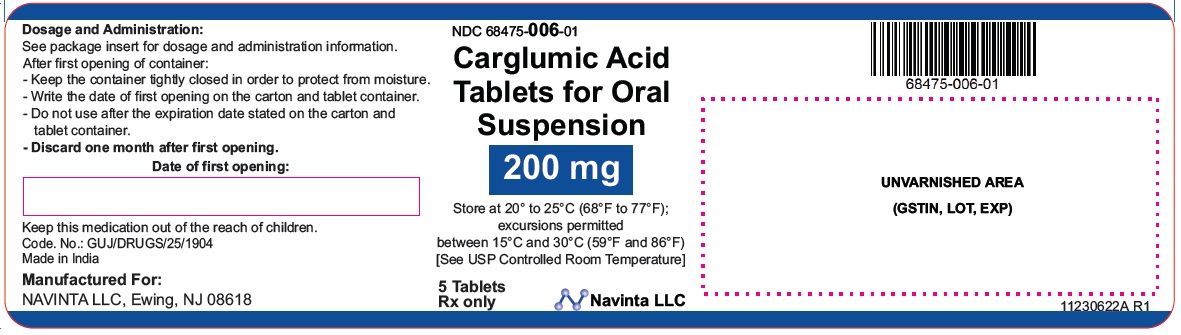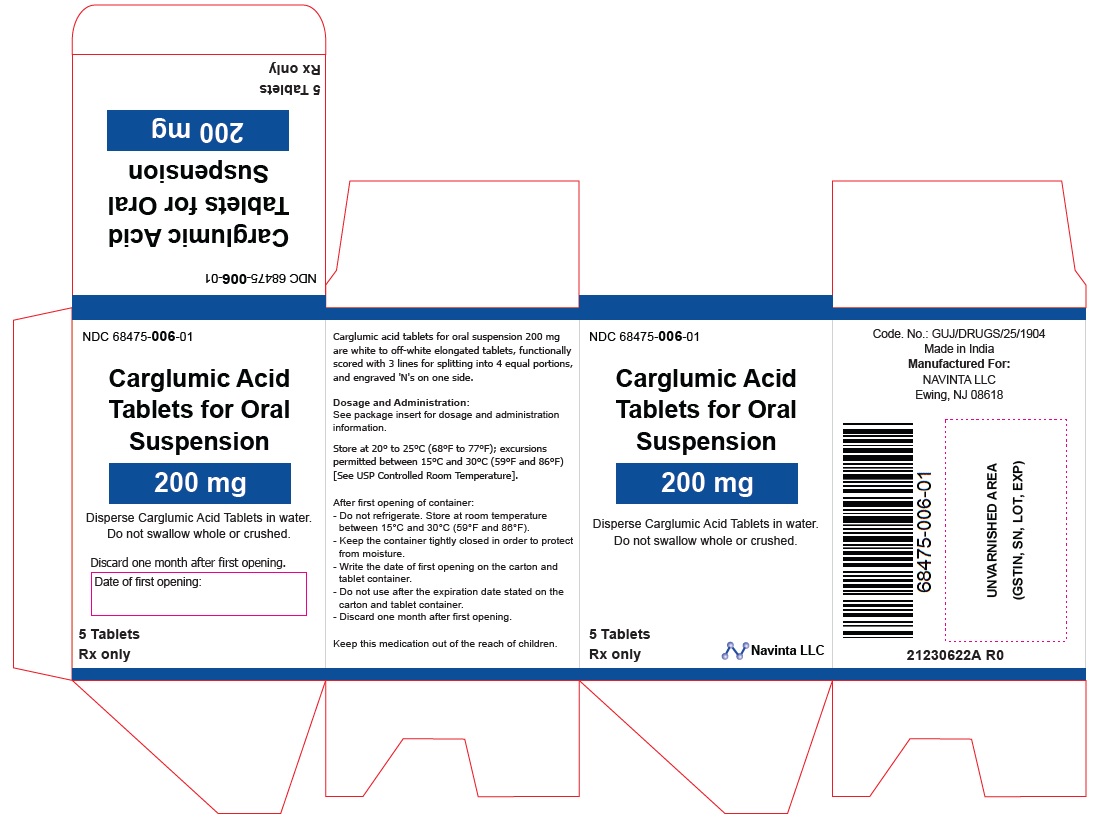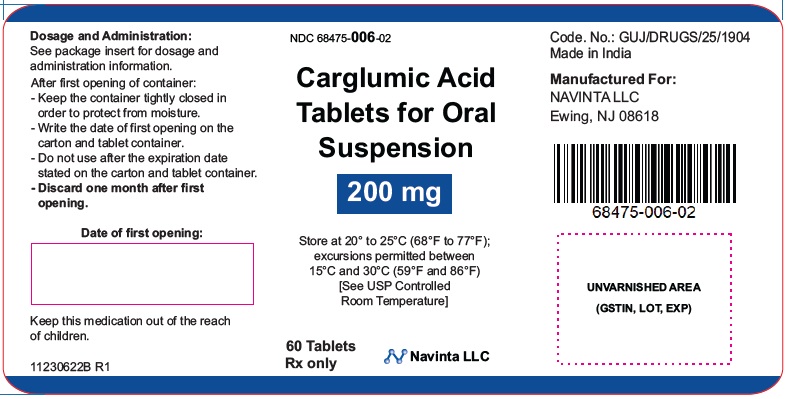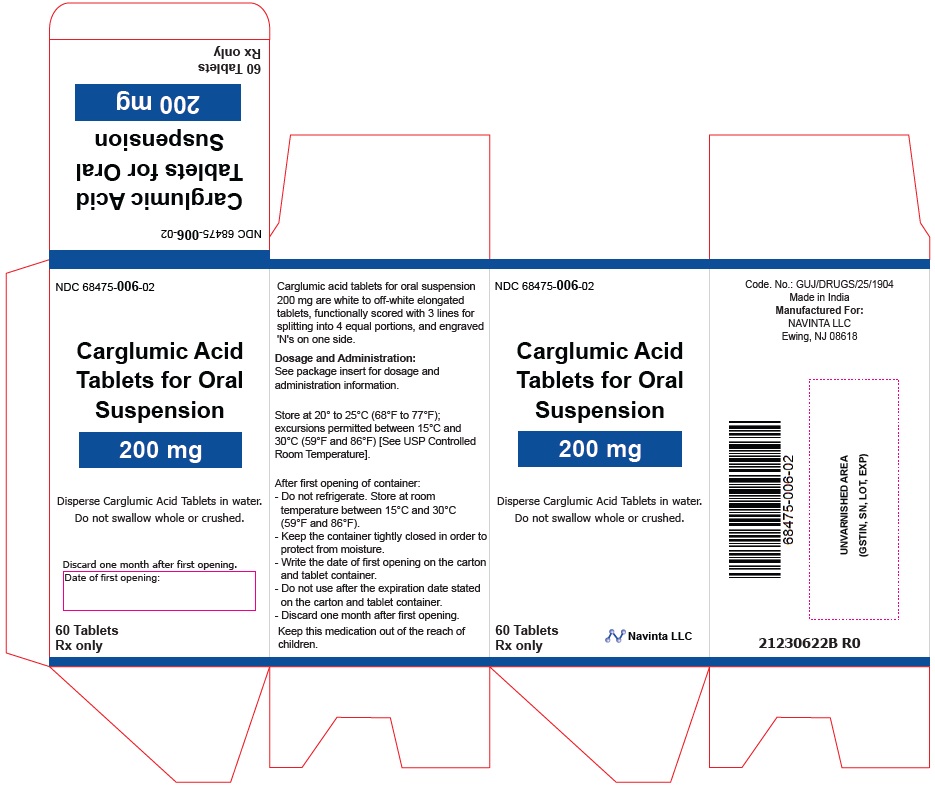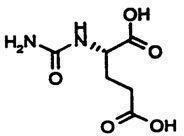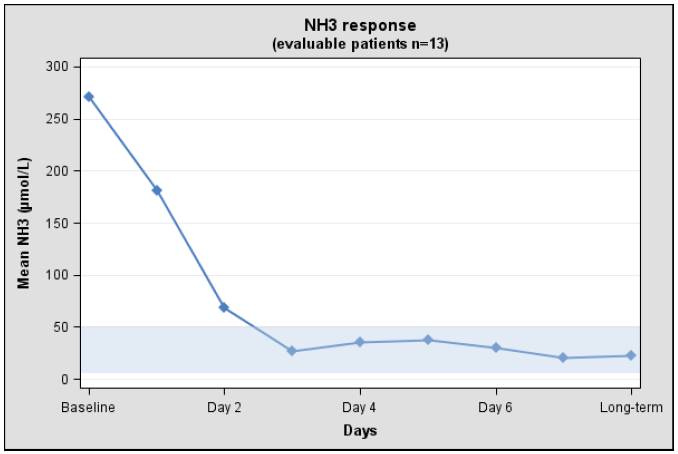 DRUG LABEL: Carglumic acid
NDC: 68475-006 | Form: TABLET, FOR SUSPENSION
Manufacturer: Navinta LLC
Category: prescription | Type: HUMAN PRESCRIPTION DRUG LABEL
Date: 20240323

ACTIVE INGREDIENTS: CARGLUMIC ACID 200 mg/1 1
INACTIVE INGREDIENTS: MICROCRYSTALLINE CELLULOSE 167.7 mg/1 1; MICROCRYSTALLINE CELLULOSE 105 100.3 mg/1 1; CROSCARMELLOSE SODIUM 25 mg/1 1; SODIUM LAURYL SULFATE 0.5 mg/1 1; SILICON DIOXIDE 1.5 mg/1 1; SODIUM STEARYL FUMARATE 5 mg/1 1

HIGHLIGHTS OF PRESCRIBING INFORMATION

These highlights do not include all the information needed to use CARGLUMIC ACID TABLETS FOR ORAL SUSPENSION safely and effectively. See full prescribing information for CARGLUMIC ACID TABLETS FOR ORAL SUSPENSION.
CARGLUMIC ACID tablets for oral suspension
Initial U.S. Approval: 2010

1 INDICATIONS AND USAGE

Carglumic acid tablets for oral suspension is a carbamoyl phosphate synthetase 1 (CPS 1) activator indicated in pediatric and adult patients as:

- Adjunctive therapy to standard of care for the treatment of acute hyperammonemia due to N-acetylglutamate synthase (NAGS) deficiency. (1.1)
- Maintenance therapy for the treatment of chronic hyperammonemia due to NAGS deficiency. (1.1)

2 DOSAGE AND ADMINISTRATION

Acute Hyperammonemia due to NAGS deficiency (2.2)

- The recommended dosage in adult and pediatric patients is 100 mg/kg to 250 mg/kg orally daily. Divide the daily dosage into 2 to 4 doses.

Chronic Hyperammonemia due to NAGS deficiency (2.2)

- The recommended dosage in adult and pediatric patients is 10 mg/kg to 100 mg/kg orally daily. Divide the daily dosage into 2 to 4 doses.

Therapeutic Monitoring for NAGS Deficiency (2.2)

- Closely monitor plasma ammonia and titrate dosage to maintain the ammonia level within normal range for the patient's age, taking into consideration their clinical condition.

Patients with Renal Impairment (2.4)

- See Full Prescribing Information for Instructions on Dosage Adjustment.

Preparation and Administration (2.5)

- Disperse carglumic acid tablets for oral suspension in water. Do not swallow whole or crushed.
- Take immediately before meals or feedings.
- For additional instructions on preparation and administration orally or through a nasogastric tube or gastrostomy tube, see the full prescribing information.

3 DOSAGE FORMS AND STRENGTHS

Tablets for oral suspension: 200 mg, functionally scored (3)

4 CONTRAINDICATIONS

None.

6 ADVERSE REACTIONS

- NAGS deficiency : Most common adverse reactions (≥13%) are vomiting, abdominal pain, pyrexia, tonsillitis, anemia, diarrhea, ear infection, infections, nasopharyngitis, hemoglobin decreased, and headache. (6.1)

To report SUSPECTED ADVERSE REACTIONS, contact Navinta LLC at 1-609-883-1135, or FDA at 1-800-FDA-1088 or www.fda.gov/medwatch.

FULL PRESCRIBING INFORMATION

1 INDICATIONS AND USAGE

1.1 Acute and Chronic Hyperammonemia due to N-acetylglutamate Synthase (NAGS) Deficiency

Carglumic acid tablets for oral suspension is indicated in adult and pediatric patients as:

• Adjunctive therapy to standard of care for the treatment of acute hyperammonemia due to NAGS deficiency.

• Maintenance therapy for the treatment of chronic hyperammonemia due to NAGS deficiency.

2 DOSAGE AND ADMINISTRATION

2.1 Important Administration Instructions

- Disperse carglumic acid tablets for oral suspension in water. Do not swallow whole or crush [see Dosage and Administration (2.5)].
- Carglumic acid tablets for oral suspension may be administered by mouth or via a nasogastric or gastrostomy tube [see Dosage and Administration (2.5)].

2.2 Recommended Dosage for Acute or Chronic Hyperammonemia due to NAGS Deficiency

Treatment Initiation

Initiate Carglumic acid tablets for oral suspension treatment as soon as the diagnosis of NAGS deficiency is suspected, which may be as soon as at birth, and supervised by a healthcare provider experienced in the treatment of metabolic disorders.

Dosage for Acute Hyperammonemia due to NAGS Deficiency

• The recommended dosage of Carglumic acid tablets for oral suspension in adult and pediatric patients for acute hyperammonemia due to NAGS deficiency is (based on actual body weight) 100 mg/kg to 250 mg/kg orally daily.

• Divide the daily dosage into 2 to 4 doses and round to the nearest 100 mg (i.e., half of a Carglumic acid tablets for oral suspension).

• During acute hyperammonemic episodes, administer Carglumic acid tablets for oral suspension with other ammonia lowering therapies, such as alternate pathway medications, hemodialysis, and protein restriction.

Dosage for Chronic Hyperammonemia due to NAGS Deficiency

• The recommended daily dosage of Carglumic acid tablets for oral suspension in adult and pediatric patients for chronic hyperammonemia due to NAGS deficiency is (based on actual body weight) 10 mg/kg to 100 mg/kg orally daily.

• Divide the daily dosage into 2 to 4 doses and round to the nearest 100 mg (i.e., half of a Carglumic acid tablets for oral suspension).

• During maintenance therapy, the concomitant use of other ammonia lowering therapies and protein restriction may be needed based on plasma ammonia levels.

Therapeutic Monitoring

Closely monitor plasma ammonia levels. Titrate the Carglumic acid tablets for oral suspension dosage to maintain the plasma ammonia level within the normal range for the patient's age, taking into consideration their clinical condition (e.g., nutritional requirements, protein intake, growth parameters, etc.).

Adjust the recommended dosage in patients with moderate or severe renal impairment [see Dosage and Administration (2.4)].

2.4 Dosage Adjustment in Patients with Renal Impairment

No dosage adjustment is warranted in patients with mild renal impairment (eGFR 60-89 mL/min/1.73 m^2). The recommended dosage of carglumic acid tablets for oral suspension in patients with moderate or severe renal impairment is shown below.

 | Moderate Renal Impairment (eGFR 30-59 mL/min/1.73 m^2) | Severe Renal Impairment (eGFR 15-19 mL/min/1.73 m^2)
Acute Hyperammonemia due to NAGS Deficiency | 50 mg/kg/day to 125 mg/kg/day divided into 2 to 4 doses and rounded to the nearest 50 mg (i.e., one-quarter of a carglumic acid tablets for oral suspension) | 15 mg/kg/day to 60 mg/kg/day divided into 2 to 4 doses and rounded to the nearest 50 mg (i.e., one-quarter of a carglumic acid tablets for oral suspension)
Chronic Hyperammonemia due to NAGS Deficiency | 5 mg/kg/day to 50 mg/kg/day divided into 2 to 4 doses and rounded to the nearest 50 mg (i.e., one-quarter of a carglumic acid tablets for oral suspension) | 2 mg/kg/day to 25 mg/kg/day divided into 2 to 4 doses and rounded to the nearest 50 mg (i.e., one-quarter of a carglumic acid tablets for oral suspension)

2.5 Preparation and Administration

Overview

- Disperse carglumic acid tablets for oral suspension in water. Do not swallow whole or crush.
- Carglumic acid tablets for oral suspension do not dissolve completely in water, and undissolved particles of the tablet may remain in the mixing container.
- Take carglumic acid tablets for oral suspension immediately before meals or feedings.
- The carglumic acid tablets for oral suspension has a slightly acidic taste.
- For all preparations, use in foods or liquids other than water has not been studied and is not recommended.

Oral Administration

For oral administration, administer Carglumic acid tablets for oral suspension as follows:

- Add a minimum of 2.5 mL of water into a small cup for each carglumic acid tablet for oral suspension or each ½ or ¼ carglumic acid tablet for oral suspension needed for the prescribed dose.
- Add the carglumic acid tablets for oral suspension to the water in the cup.
- Carefully stir the tablet and water mixture.
- Swallow the mixture immediately. Pieces of the tablet may remain in the cup.
- Rinse the cup with additional water and swallow the mixture immediately. Repeat as needed until no pieces of the tablet are left in the cup.

Use of an Oral Syringe for Oral Administration

For administration via an oral syringe, administer Carglumic acid tablets for oral suspension as follows:

- Add a minimum of 2.5 mL of water into a small cup for each Carglumic acid tablets for oral suspension or each ½ or ¼ Carglumic acid tablets for oral suspension needed for the prescribed dose.
- Add the Carglumic acid tablets for oral suspension to the water in the cup.
- Carefully stir the tablet and water mixture.
- Draw up the mixture in an oral syringe and administer immediately. Pieces of the tablet may remain in the oral syringe.
- Refill the oral syringe with a minimum volume of water (1 mL to 2 mL) and administer immediately.
- Flush the oral syringe again, as needed, until no pieces of the tablet are left in the syringe.

Use of Nasogastric Tube (NG Tube) or Gastrostomy Tube (G-Tube) for Feeding Tube Administration

For patients who have a NG tube or G-tube in place, administer carglumic acid tablets for oral suspension as follows:

- Add a minimum of 2.5 mL of water into a small cup for each carglumic acid tablet for oral suspension or each ½ or ¼ carglumic acid tablet for oral suspension needed for the prescribed dose.
- Add the carglumic acid tablets for oral suspension to the water in the cup.
- Carefully stir the tablet and water mixture.
- Draw up the mixture into a catheter-tip syringe.
- Administer the mixture immediately through the NG tube or G-tube. Pieces of the tablet may remain in the catheter-tip syringe or the feeding tube.
- Flush immediately with 1 to 2 mL of additional water to clear the NG tube or G-tube.
- Flush the NG tube or G-tube again, as needed, until no pieces of the tablet are left in the syringe or the feeding tube.

3 DOSAGE FORMS AND STRENGTHS

Carglumic acid tablets for oral suspension 200 mg are white to off-white elongated tablets, functionally scored with 3 lines (for splitting into 4 equal portions) and engraved "N" on one side.

4 CONTRAINDICATIONS

None

6 ADVERSE REACTIONS

6.1 Clinical Trials Experience

Because clinical trials are conducted under widely varying conditions, adverse reaction rates observed in the clinical trials of a drug cannot be directly compared to rates in the clinical trials of another drug and may not reflect the rates observed in practice.

Acute and Chronic Hyperammonemia due to NAGS Deficiency

In a retrospective case series of 23 NAGS deficiency patients treated with Carglumic acid tablets for oral suspension, 17 of the 23 patients reported an adverse reaction. The most common adverse reactions (occurring in ≥ 13% of patients) were vomiting, abdominal pain, pyrexia, tonsillitis, anemia, diarrhea, ear infection, infections, nasopharyngitis, hemoglobin decreased, and headache.

Table 1 summarizes adverse reactions occurring in 2 or more patients treated with carglumic acid tablets for oral suspension.

Table 1: Adverse Reactions Reported in ≥ 2 Patients with NAGS deficiency Treated with Carglumic Acid Tablets for Oral Suspension in the Retrospective Case Series
Adverse Reaction | Number of Patients (N) (%)
Vomiting | 6 (26)
Abdominal pain | 4 (17)
Pyrexia | 4 (17)
Tonsillitis | 4 (17)
Anemia | 3 (13)
Diarrhea | 3 (13)
Ear infection | 3 (13)
Infections | 3 (13)
Nasopharyngitis | 3 (13)
Hemoglobin decreased | 3 (13)
Headache | 3 (13)
Dysgeusia | 2 (9)
Asthenia | 2 (9)
Hyperhidrosis | 2 (9)
Influenza | 2 (9)
Pneumonia | 2 (9)
Weight decreased | 2 (9)
Anorexia | 2 (9)
Somnolence | 2 (9)
Rash | 2 (9)

6.2 Postmarketing Experience

The following adverse reactions have been identified during postapproval use of Carglumic acid tablets for oral suspension. Because these reactions are reported voluntarily from a population of uncertain size, it is not always possible to reliably estimate their frequency or to establish a causal relationship to drug exposure.

Psychiatric disorders: mania

Skin and subcutaneous tissue disorders: pruritus, rash including rash erythematous, rash maculopapular, rash pustular

8 USE IN SPECIFIC POPULATIONS

8.1 Pregnancy

Risk Summary

Although rare case reports of carglumic acid tablets for oral suspension use in pregnant women are insufficient to inform a drug-associated risk of major birth defects, miscarriage, or adverse maternal or fetal outcomes, untreated NAGS deficiency can result in irreversible neurologic damage and death in pregnant women (see Clinical Considerations).

In an animal reproduction study, decreased survival and growth occurred in offspring born to rats that received carglumic acid at a dose approximately 38 times the maximum reported human maintenance dose.

The estimated background risk of major birth defects and miscarriage for the indicated population is unknown. All pregnancies have a background risk of birth defect, miscarriage, or other adverse outcomes. In the U.S. general population, the estimated background risk of major birth defects and miscarriage in clinically recognized pregnancies is 2% to 4% and 15% to 20%, respectively.

Clinical Considerations

Disease-associated maternal and/or embryo/fetal risk

Pregnant women with urea cycle disorders may experience an increase in catabolic stress which can trigger a hyperammonemic crisis both in the intrapartum and in the post-partum (3 - 14 days post-partum) periods. Maternal complications related to hyperammonemic crisis can include neurological impairment, coma and in some cases death.

Data

Animal Data

No effects on embryo-fetal development were observed in pregnant rats treated with up to 2000 mg/kg/day (approximately 38 times the maximum reported human maintenance dose [100 mg/kg/day] based on AUC [area under the plasma concentration-time curve]) from two weeks prior to mating through organogenesis or in pregnant rabbits treated with up to 1000 mg/kg/day (approximately 6 times the maximum reported human maintenance dose [100 mg/kg/day] based on AUC) during organogenesis.

In a pre- and post-natal developmental study, female rats received oral carglumic acid from organogenesis through lactation at doses of 500 mg/kg/day and 2000 mg/kg/day. Decreased growth of offspring was observed at 500 mg/kg/day and higher (approximately 38 times the maximum reported human maintenance dose [100 mg/kg/day] based on AUC), and reduction in offspring survival during lactation was observed at 2000 mg/kg/day (approximately 38 times the maximum reported human maintenance dose [100 mg/kg/day] based on AUC). No effects on physical and sexual development, learning and memory, or reproductive performance were observed through maturation of the surviving offspring at maternal doses up to 2000 mg/kg/day. The high dose (2000 mg/kg/day) produced maternal toxicity (impaired weight gain and approximately 10% mortality).

8.2 Lactation

Risk Summary

It is not known whether carglumic acid is present in human milk. There are no available data on the effects of carglumic acid on the breastfed infant or the effects on milk production. Carglumic acid is present in milk from treated rats. When a drug is present in animal milk, it is likely that the drug will be present in human milk.

The developmental and health benefits of breastfeeding should be considered along with the mother's clinical need for carglumic acid tablets for oral suspension and any potential adverse effects on the breastfed child from carglumic acid tablets for oral suspension or from the underlying maternal condition.

8.4 Pediatric Use

The safety and effectiveness of carglumic acid tablets for oral suspension for the treatment of pediatric patients (birth to 17 years of age) with acute or chronic hyperammonemia due to NAGS deficiency have been established, and the information on these uses are discussed throughout the labeling. There are insufficient data to determine if there is a difference in clinical or biochemical responses between adult and pediatric patients treated with Carglumic acid tablets for oral suspension.

8.5 Geriatric Use

Clinical studies of Carglumic acid tablets for oral suspension did not include patients 65 years of age and older to determine whether they respond differently from younger patients.

8.6 Renal Impairment

Plasma concentrations of carglumic acid increased in patients with renal impairment [see Clinical Pharmacology (12.3)]. Reduce the carglumic acid tablets for oral suspension dosage in patients with moderate or severe renal impairment [see Dosage and Administration (2.4)]. The pharmacokinetics of carglumic acid have not been evaluated in patients with end stage renal disease.

10 OVERDOSAGE

One patient treated with 650 mg/kg/day of Carglumic acid tablets for oral suspension developed symptoms resembling monosodium glutamate intoxication-like syndrome and characterized by tachycardia, profuse sweating, increased bronchial secretion, increased body temperature, and restlessness. These symptoms resolved upon reduction of the dose.

11 DESCRIPTION

Carglumic acid tablets for oral suspension contain 200 mg of carglumic acid. Carglumic acid, the active substance, is a carbamoyl phosphate synthetase 1 (CPS 1) activator and is soluble in dimethyl formamide and sparingly soluble in water.

The chemical name of carglumic acid is N-carbamoyl-L-glutamic acid or (2S)-2-(carbamoylamino) pentanedioic acid. The empirical formula is C6H10N2O5 and the molecular weight is 190.16.

The structural formula is:

The inactive ingredients of carglumic acid tablets for oral suspension are croscarmellose sodium, microcrystalline cellulose, sodium lauryl sulfate, colloidal silicon dioxide and sodium stearyl fumarate.

12 CLINICAL PHARMACOLOGY

12.1 Mechanism of Action

Carglumic acid is a synthetic structural analogue of N-acetylglutamate (NAG) which is produced from glutamate and acetyl-CoA in a reaction catalyzed by N-acetylglutamate synthase (NAGS), a mitochondrial liver enzyme. NAG acts as an essential allosteric activator of carbamoyl phosphate synthetase 1 (CPS 1), a mitochondrial liver enzyme which catalyzes the first reaction of the urea cycle. The urea cycle, whose role is the disposition of ammonia, includes a series of biochemical reactions in the liver resulting in the conversion of ammonia into urea, which is then excreted through the urine. Carglumic acid acts as a CPS1 activator, improves or restores the function of the urea cycle, and facilitates ammonia detoxification and urea production.

12.2 Pharmacodynamics

In a retrospective review of the clinical course in 23 patients with NAGS deficiency, carglumic acid reduced plasma ammonia levels within 24 hours when administered with and without concomitant ammonia lowering therapies. No dose-response relationship has been identified.

Cardiac Electrophysiology

The effect of carglumic acid was evaluated in a Phase 1, randomized study in 76 healthy volunteers. The study suggests a lack of clinically relevant QT prolongation effect at the highest therapeutic dose level (250 mg/kg/day).

12.3 Pharmacokinetics

The pharmacokinetics of carglumic acid in healthy subjects following an intravenous (IV) infusion over 2 hours at 8 mg/kg or an oral administration at 100 mg/kg are summarized in Table 3.

Table 3: Mean (SD) Pharmacokinetic Parameter Values of Carglumic Acid in Healthy Subjects
PK parameter | IV infusion 8 mg/kg (N=10) | Oral 100 mg/kg (N=12)
Cmax (ng/mL) | 8613 (558) | 3284 (321)
Tmax (hr)# | 2 (1-2) | 3 (2-4)
AUC (ng*hr/mL) | 24501 (1613) | 31426 (2150)
T1/2 (hr) | 31 (3) | 25 (2)
CL (L/hr/kg) | 0.34 (0.02) | N/A
Vd (L/kg) | 15 (1) | N/A
# Median (range); N/A, not applicable.

Absorption

Following an oral administration of Carglumic acid tablets for oral suspension 100 mg/kg in healthy subjects, the absolute bioavailability was approximately 10%.

Distribution

Carglumic acid is not bound to plasma proteins.

Elimination

Carglumic acid is predominantly excreted by the kidneys as unchanged product.

Metabolism

A proportion of carglumic acid may be metabolized by the intestinal bacterial flora.

The likely end product of carglumic acid metabolism is carbon dioxide, eliminated through the lungs.

Excretion

Following an oral administration of radiolabeled carglumic acid tablets for oral suspension at 100 mg/kg, 9% of the dose is excreted unchanged in the urine and up to 60% of the dose is recovered unchanged in the feces.

Specific Populations

Patients with Renal Impairment

The pharmacokinetics of carglumic acid in subjects with renal impairment were compared with healthy subjects with normal renal function following oral administration of a single dose of carglumic acid tablets for oral suspension 40 mg/kg or 80 mg/kg. The Cmax and AUC0-t of carglumic acid are summarized in Table 4. The geometric mean ratio (90% CI) of Cmax in subjects with mild, moderate, and severe renal impairment relative to those in their matched control subjects with normal renal function were approximately 1.3 (0.95, 1.86), 2.0 (1.62, 2.50), and 4.4 (3.11, 6.28) respectively. The geometric mean ratio (90% CI) of AUC0-t in subjects with mild, moderate, and severe renal impairment relative to those in their matched control subjects with normal renal function were approximately 1.4 (1.09, 1.73), 2.8 (2.27, 3.47), and 6.9 (5.21, 9.24), respectively [see Dosage and Administration (2.4)].

Table 4: Mean (SD) Cmax and AUC0-tof Carglumic Acid Following Single Oral Dose Administration of carglumic acid tablets for oral suspension 80 mg/kg or 40 mg/kg in Subjects with Renal Impairment and Matched Healthy Control Subjects with Normal Renal Function
PK Parameters | Normal Renal Function1a: eGFR ≥90 mL/min/1.73m^2 (N=8) | Mild Renal Impairment: eGFR 60-89 mL/min/1.73m^2 (N=8) |  | Moderate Renal Impairment: eGFR 30-59 mL/min/1.73m^2 (N=8) | Normal Renal Function1b: eGFR ≥90 mL/min/1.73m^2 (N=8) | Severe Renal Impairment: eGFR 15-29 mL/min/1.73m^2 (N=8)
PK Parameters |  | 80 mg/kg |  |  | 40 mg/kg
Cmax (ng/mL) | 2983 (552) | 4310 (1937) |  | 6129 (1854) | 1890 (901) | 8377 (3815)
AUC0-t (ng*hr/mL) | 28313 (6204) | 39545 (12109) |  | 79766 (19708) | 20212 (6186) | 143075 (55910)
Treatment groups 1a and 1b represent two separate matched control groups of healthy subjects with normal renal function.

Drug Interaction Studies

Based on in vitro studies, carglumic acid is not an inducer of CYP1A1/2, CYP2B6, CYP2C, and CYP3A4/5 enzymes, and not an inhibitor of CYP1A2, CYP2A6, CYP2B6, CYP2C8, CYP2C9, CYP2C19, CYP2D6, CYP2E1, and CYP3A4/5 enzymes.

Based on in vitro studies, carglumic acid is a substrate of the human OAT1 transporter. Carglumic acid is not a substrate of MDR1, BCRP, MATE1, MATE2-K, OAT1, OAT3, OATP1B1, OATP1B3, OCT1, and OCT2. Carglumic acid is not an inhibitor of human BSEP, BCRP, MDR1, MATE1, MATE2-K, OAT1, OAT3, OATP1B1, OATP1B3, OCT1, and OCT2 transporters.

13 NONCLINICAL TOXICOLOGY

13.1 Carcinogenesis, Mutagenesis, Impairment of Fertility

The carcinogenic potential of carglumic acid was assessed in a 2-year carcinogenicity study in rats. Carglumic acid was not tumorigenic at oral doses up to 1000 mg/kg/day (approximately 34 times the maximum reported human maintenance dose [100 mg/kg/day] based on AUC).

Carglumic acid was negative in the Ames test, chromosomal aberration assay in human lymphocytes, and the in vivo micronucleus assay in rats.

There were no effects on fertility or reproductive performance in female rats at oral doses up to 2000 mg/kg/day (approximately 38 times the maximum reported human maintenance dose [100 mg/kg/day] based on AUC). In a separate study, mating and fertility were unaffected in male rats at oral doses up to 1000 mg/kg/day (approximately 34 times the maximum reported human maintenance dose [100 mg/kg/day] based on AUC).

14 CLINICAL STUDIES

14.1 Acute and Chronic Hyperammonemia due to NAGS Deficiency

The efficacy of carglumic acid tablets for oral suspension in the treatment of acute and chronic hyperammonemia due to NAGS deficiency was evaluated in a retrospective case series of 23 NAGS deficiency patients treated with Carglumic acid tablets for oral suspension over a median duration of 7.9 years (range 0.6 to 20.8 years). For acute treatment, patients received Carglumic acid tablets for oral suspension at 100 mg/kg/day to 250 mg/kg/day orally administered in 2 to 4 divided doses. For maintenance treatment, the dosage was reduced over time based on plasma ammonia level and clinical responses.

The baseline characteristics of the patient population are shown in Table 5.

Table 5: Baseline Characteristics of 23 NAGS Deficiency Patients Treated with Carglumic Acid Tablets for Oral Suspension
Patients
N=23
Sex | Male | 14 (61%)
Sex | Female | 9 (39%)
Age at initiation of carglumic acid tablets for oral suspension therapy (years) | Mean (SD) | 2 (4)
Age at initiation of carglumic acid tablets for oral suspension therapy (years) | Min to Max | 0 - 13
Age groups at initiation of carglumic acid tablets for oral suspension therapy | <30 days | 9 (39%)
Age groups at initiation of carglumic acid tablets for oral suspension therapy | >30 days - 11 months | 9 (39%)
Age groups at initiation of carglumic acid tablets for oral suspension therapy | ≥1 - 13 years | 5 (22%)
NAGS gene mutations by DNA testing | Homozygous | 14 (61%)
NAGS gene mutations by DNA testing | Heterozygous | 4 (17%)
NAGS gene mutations by DNA testing | Not available | 5 (22%)
Patients current treatment status | On-going | 18 (78%)
Patients current treatment status | Discontinued | 5 (22%)

The clinical and biochemical data in the 23-patient case series were retrospectively collected, unblinded, and uncontrolled and preclude formal statistical testing. Short-term efficacy was evaluated using mean and median change in plasma ammonia levels from baseline to days 1 to 3. Persistence of the effect was evaluated using long-term mean and median change in plasma ammonia level. Of the 23 NAGS deficiency patients in the case series, 13 patients had documented plasma ammonia levels prior to carglumic acid tablets for oral suspension treatment and after long-term treatment with carglumic acid tablets for oral suspension and were evaluable.

Table 6 summarizes the plasma ammonia levels at baseline, days 1 to 3 post- carglumic acid tablets for oral suspension treatment, and long-term carglumic acid tablets for oral suspension treatment (mean 8 years) in the 13 evaluable patients.

All 13 patients had increased plasma ammonia levels at baseline (mean 271 micromol/L; normal range: 5 to 50 micromol/L). By day 3 and with long-term treatment, normal plasma ammonia levels were attained (Table 6).

Table 6: Plasma Ammonia Levels in NAGS Deficiency Patients at Baseline and After Treatment with Carglumic Acid Tablets for Oral Suspension
Time point | Patients (N = 13) | Ammonia level (micromol/L)
Baseline (prior to first dose of carglumic acid tablets for oral suspension) | N | 13
Baseline (prior to first dose of carglumic acid tablets for oral suspension) | Mean (SD) | 271 (359)
Baseline (prior to first dose of carglumic acid tablets for oral suspension) | Median | 157
Baseline (prior to first dose of carglumic acid tablets for oral suspension) | Range | 72-1428
Baseline (prior to first dose of carglumic acid tablets for oral suspension) | Missing Data | 0
Day 1 | N | 10
Day 1 | Mean (SD) | 181 (358)
Day 1 | Median | 65
Day 1 | Range | 25-1190
Day 1 | Missing Data | 3
Day 2 | N | 8
Day 2 | Mean (SD) | 69 (78)
Day 2 | Median | 44
Day 2 | Range | 11-255
Day 2 | Missing Data | 5
Day 3 | N | 5
Day 3 | Mean (SD) | 27 (11)
Day 3 | Median | 25
Day 3 | Range | 12-42
Day 3 | Missing Data | 8
Long-term treatment (mean duration 8 years; median duration 6 years; range 1-16 years based on last available value while on carglumic acid tablets for suspension treatment.) | N | 13
Long-term treatment (mean duration 8 years; median duration 6 years; range 1-16 years based on last available value while on carglumic acid tablets for suspension treatment.) | Mean (SD) | 23 (7)
Long-term treatment (mean duration 8 years; median duration 6 years; range 1-16 years based on last available value while on carglumic acid tablets for suspension treatment.) | Median | 24
Long-term treatment (mean duration 8 years; median duration 6 years; range 1-16 years based on last available value while on carglumic acid tablets for suspension treatment.) | Range | 9-34
Long-term treatment (mean duration 8 years; median duration 6 years; range 1-16 years based on last available value while on carglumic acid tablets for suspension treatment.) | Missing Data | 0

The mean plasma ammonia level at baseline and the decline that is observed after treatment with carglumic acid tablets for oral suspension in 13 evaluable patients with NAGS deficiency is illustrated in Figure 1.

Figure 1: Mean Plasma Ammonia in 13 Evaluable NAGS Deficiency Patients at Baseline and After Treatment with carglumic acid tablets for oral suspension

16 HOW SUPPLIED/STORAGE AND HANDLING

How Supplied

Carglumic acid tablets for oral suspension 200 mg are white to off-white elongated tablets, functionally scored with 3 lines for splitting into 4 equal portions, and engraved 'N's on one side.

Carglumic acid tablets for oral suspension is supplied in a high-density polyethylene bottle with a child resistant polypropylene cap and desiccant unit. Each bottle contains either 5 or 60 tablets.

Bottle of 5 tablets: NDC 68475-006-01

Bottle of 60 tablets: NDC 68475-006-02

Storage

Store at 20° to 25°C (68°F to 77°F); excursions permitted to 15°C to 30°C (59°F to 86°F) [See USP Controlled Room Temperature].

After first opening of the bottle:

- Store at room temperature between 15°C and 30°C (59°F and 86°F). Do not refrigerate.
- Keep the bottle tightly closed between openings in order to protect from moisture.
- Write the date of opening on the bottle.
- Do not use carglumic acid tablets for oral suspension after the expiration date stated on the bottle.
- Discard bottle one month after first opening.

17 PATIENT COUNSELING INFORMATION

Advise the patient to read the FDA-approved patient labeling (Instructions for Use).

Advise the patient or caregiver on the following:

Preparation and Administration [see Dosage and Administration (2.5)]

- Disperse carglumic acid tablets for oral suspension in water. Do not swallow whole or crushed.
- Take carglumic acid tablets for oral suspension immediately before meals or feedings.
- Carglumic acid tablets for oral suspension dispersed in water can be administered orally or via a nasogastric tube or gastrostomy tube, as described in the Instructions for Use .

Storage [see How Supplied/Storage and Handling (16)]

- Store at 20° to 25°C (68° to 77°F); excursions permitted to 15° to 30°C (59° to 86°F) [See USP Controlled Room Temperature]
- After first opening of the bottle: Do not refrigerate. Store at room temperature between 15° to 30°C (59° to 86°F). Keep the bottle tightly closed in order to protect from moisture. Write the date of opening on the bottle.
- Discard bottle one month after first opening. Do not use carglumic acid tablets for oral suspension after the expiration date stated on the bottle.

Manufactured for:

Navinta LLC

1499 lower Ferry Road, Ewing,

NJ 08618

Revised: 03/2024

31230622 R1

INSTRUCTIONS FOR USE

Carglumic Acid Tablets for Oral Suspension

Important information:

- Carglumic acid tablet for oral suspension must be mixed in water before taking. Carglumic acid tablets for oral suspension should not be mixed in any other food or liquid.
- Do not swallow carglumic acid tablets for oral suspension whole.
- Do not crush carglumic acid tablets for oral suspension.
- Take carglumic acid tablets for oral suspension right before meals or feedings.
- The carglumic acid tablet for oral suspension and water mixture has a slightly sour taste.

You may need to ask your healthcare provider or pharmacist for a medicine cup to measure the correct amount of water you will need to prepare the dose of carglumic acid tablets for oral suspension.

The Carglumic acid tablets for oral suspension has 3 lines used for splitting the tablet into 4 equal parts in order to get the prescribed dose. Ask your healthcare provider if you have any questions about how to split the tablet the right way or have any questions about the prescribed dose.

Taking carglumic acid tablets for oral suspension by mouth using a cup:

Children and Adults

1. Add a minimum 2.5 mL of water into a small cup for each carglumic acid tablet for oral suspension, or each ½ or ¼ carglumic acid tablet for oral suspension, needed for the prescribed dose. For example:
  - If the prescribed dose is 2 carglumic acid tablets for oral suspension, add a minimum of 5 mL of water into the cup.
  - If the prescribed dose is 2 and a ¼ carglumic acid tablets for oral suspension, add a minimum of 7.5 mL of water into the cup.
  - If the prescribed dose is 2 and a ½ carglumic acid tablets for oral suspension, add a minimum of 7.5 mL of water into the cup.
  - Ask your healthcare provider if you are not sure of how much water you should use for the prescribed dose of carglumic acid tablets for oral suspension
2. Place the prescribed number of carglumic acid tablets for oral suspension into the water in the cup.
3. Carefully stir the carglumic acid tablet for oral suspension and water mixture in the cup to avoid spilling the mixture. Carglumic acid tablets for oral suspension do not dissolve completely in water.
4. Swallow the carglumic acid tablet for oral suspension and water mixture right away.
5. Pieces of the tablet may remain in the cup. Add more water to the cup to rinse the cup and swallow the mixture right away.
6. Repeat step 5 until there are no pieces of the tablet left in the cup.

Taking carglumic acid tablets for oral suspension by mouth using an oral syringe:

Children

1. Add a minimum of 2.5 mL of water into a small cup for each carglumic acid tablet for oral suspension, or each ½ or ¼ carglumic acid tablet for oral suspension, needed for the prescribed dose. For Example:
  - If the prescribed dose is 2 carglumic acid tablets for oral suspension, add a minimum of 5 mL of water into the cup.
  - If the prescribed dose is 2 and a ¼ carglumic acid tablets for oral suspension, add a minimum of 7.5 mL of water into the cup.
  - If the prescribed dose is 2 and a ½ carglumic acid tablets for oral suspension, add a minimum of 7.5 mL of water into the cup.
  - Ask your healthcare provider if you are not sure of how much water you should use for the prescribed dose of carglumic acid tablets for oral suspension.
2. Place the prescribed number of carglumic acid tablets for oral suspension into the water in the cup.
3. Carefully stir the carglumic acid tablet for oral suspension and water mixture in the cup to avoid spilling the mixture. Carglumic acid tablets for oral suspension do not dissolve completely in water.
4. Draw up all of the carglumic acid tablet for oral suspension and water mixture in the cup into an oral syringe.
5. Give your child the carglumic acid tablet for oral suspension and water mixture right away by placing the tip of the oral syringe along the inner cheek of their mouth, on either the right or left side. Slowly push all the way down on the plunger to give the medicine.
6. Pieces of the tablet may remain in the oral syringe. Refill the oral syringe with a minimum of 1 mL to 2 mL of water and give your child the mixture right away.
7. Repeat step 6 until there are no pieces of the tablet left in the oral syringe.

Giving carglumic acid tablets for oral suspension through a nasogastric (NG) tube or gastrostomy tube (G-tube):

Children and Adults

1. Add a minimum of 2.5 mL of water into a small cup for each carglumic acid tablet for oral suspension, or each ½ or ¼ carglumic acid tablet for oral suspension, needed for the prescribed dose. For example:
  - If the prescribed dose is 2 carglumic acid tablets for oral suspension, add a minimum of 5 mL of water into the cup.
  - If the prescribed dose is 2 and a ¼ carglumic acid tablets for oral suspension, add a minimum of 7.5 mL of water into the cup.
  - If the prescribed dose is 2 and a ½ carglumic acid tablets for oral suspension, add a minimum of 7.5 mL of water into the cup.
  - Ask your healthcare provider if you are not sure of how much water you should use for the prescribed dose of carglumic acid tablets for oral suspension.
2. Place the prescribed number of carglumic acid tablets for oral suspension into the water in the cup.
3. Carefully stir the carglumic acid tablet for oral suspension and water mixture in the cup to avoid spilling the mixture. Carglumic acid tablets for oral suspension do not dissolve completely in water.
4. Draw up all of the carglumic acid tablet for oral suspension and water mixture in the cup into a catheter-tip syringe.
5. Connect the catheter-tip syringe to the NG tube or G-tube.
6. Give the carglumic acid tablet for oral suspension and water mixture through the NG tube or G-tube right away.
7. Pieces of the tablet may remain in the catheter-tip syringe or NG tube or G-tube.
8. Refill the catheter-tip syringe with 1 mL to 2 mL of water and flush the NG tube or G-tube right away.
9. Repeat step 8 until there are no pieces of the tablet left in the catheter-tip syringe or NG tube or G-tube.

How should I store carglumic acid tablets for oral suspension?

- Before opening, store carglumic acid tablets for oral suspension at controlled room temperature between 68°F to 77°F (20°C to 25°C) in the bottle it comes in.
- After opening, store carglumic acid tablets for oral suspension at room temperature between 59°F to 86°F (15°C to 30°C). Do not store carglumic acid tablets for oral suspension in a refrigerator after opening.
  - Keep carglumic acid tablets for oral suspension in a tightly closed bottle to protect the tablets from moisture.
  - Write the date the carglumic acid tablet for oral suspension bottle is opened on the bottle label. Throw away any unused tablets one month after opening the bottle.
- Do not use carglumic acid tablets for oral suspension after the expiration date on the bottle.
- Keep carglumic acid tablets for oral suspension and all medicines out of the reach of children.

This Instructions for Use has been approved by the U.S. Food and Drug Administration.

Manufactured for:

Navinta LLC

1499 lower Ferry Road, Ewing,

NJ 08618

Revised: 03/2024

31230622 R1

PACKAGE LABEL.PRINCIPAL DISPLAY PANEL

Bottle label - 5 Tablets in Bottle

NDC 68475-006-01

Carglumic Acid

Tablets for Oral

Suspension

200 mg

Store at 20° to 25°C (68°F to 77°F);

excursions permitted between 15°C

and 30°C (59°F and 86°F)

[See USP Controlled Room Temperature].

5 Tablets

Rx only

Navinta LLC

Carton label - 5 Tablets in Bottle

NDC 68475-006-01

Carglumic Acid

Tablets for Oral

Suspension

200 mg

Disperse Carglumic Acid Tablets in water.

Do not swallow whole or crushed.

5 Tablets

Rx only

Navinta LLC

Bottle label - 60 Tablets in Bottle

NDC 68475-006-02

Carglumic Acid

Tablets for Oral

Suspension

200 mg

Store at 20° to 25°C (68°F to 77°F);

excursions permitted between 15°C

and 30°C (59°F and 86°F).

[See USP Controlled Room Temperature].

60 Tablets

Rx only

Navinta LLC

Carton label - 60 Tablets in Bottle

NDC 68475-006-02

Carglumic Acid

Tablets for Oral

Suspension

200 mg

Disperse Carglumic Acid Tablets in water.

Do not swallow whole or crushed.

60 Tablets

Rx only

Navinta LLC